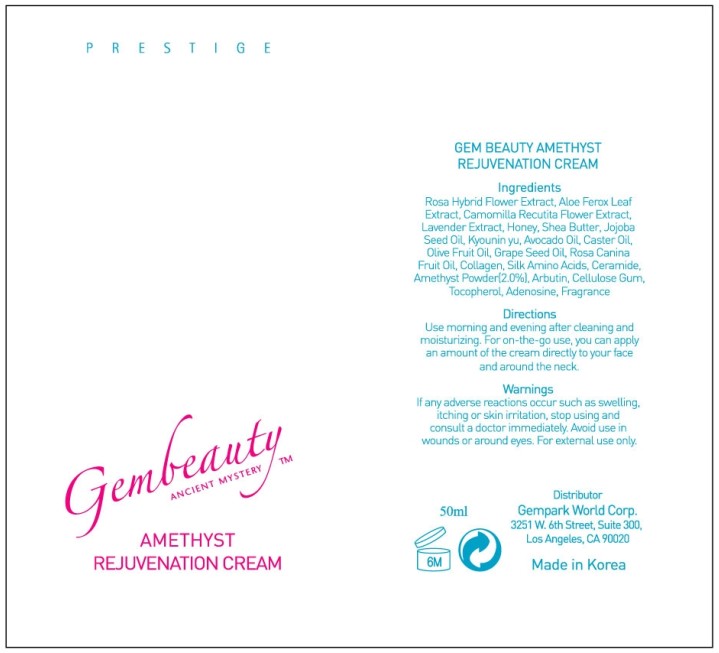 DRUG LABEL: GEM BEAUTY AMETHYST REJUVENATION CREAM
NDC: 50030-003 | Form: CREAM
Manufacturer: GEMPARK CO LTD
Category: otc | Type: HUMAN OTC DRUG LABEL
Date: 20091109

ACTIVE INGREDIENTS: ALOE VERA FLOWER 9.15 mL/50 mL

ACTIVE INGREDIENT

INGREDIENTS:

Rosa Hybrid Flower Extract, Aloe Ferox Leaf Extract, Camomilla Recutita Flower Extract, Lavender Extract, Honey, Shea Butter, Jojoba Seed Oil, Apricot Seed Oil, Avocado Oil, Caster Oil, Fruit Oil, Collagen, Silk Amino Acids, Ceramide, Amethyst Powder, Arbutin, Cellulose Gum, Tocopherol, Adenosine, Fragrance

WARNINGS:

If any adverse reactions occur such as swelling, itching or skin irritation, stop using and consult a doctor immediately. Avoid use in wounds or around eyes. For external use only.

DIRECTIONS:

Use morning and evening after cleaning and moisturizing. For on-the-go use, you can apply an amount of the cream directly to your face and around the neck.

STORAGE:

Keep out of reach of children. Store in a cool place and avoid excessive heat. Seal tightly for further use. Do not use if seal under cap is broken or missing.

DO NOT USE

EXPIRATION:

Do not use if older than eighteen months from manufacture. It would be best to use within six months once the seal is opened. The date of manufacture is separately marked.